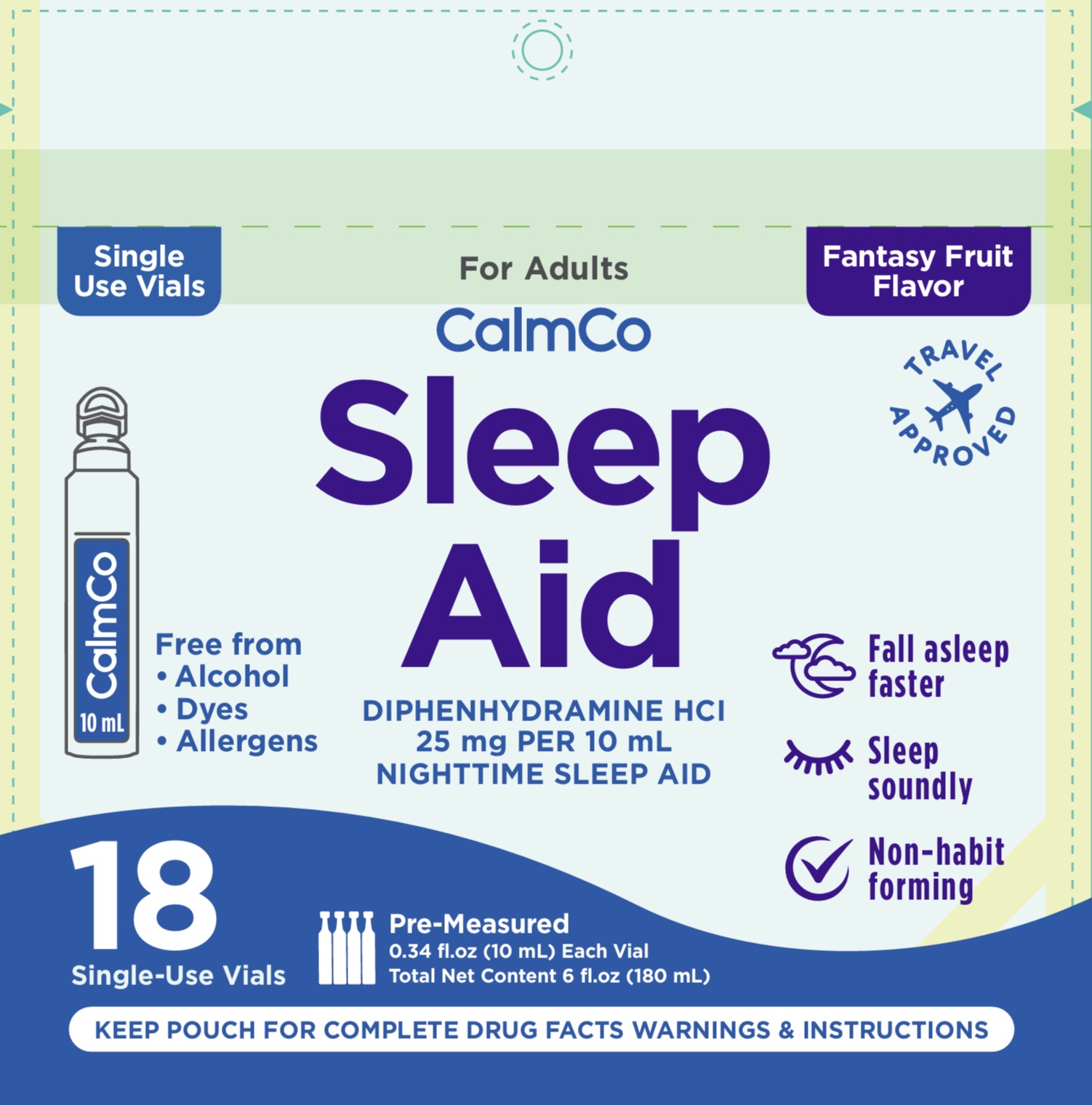 DRUG LABEL: Calmco
NDC: 73282-2525 | Form: SOLUTION
Manufacturer: CalmCo LLC
Category: otc | Type: HUMAN OTC DRUG LABEL
Date: 20251229

ACTIVE INGREDIENTS: DIPHENHYDRAMINE HYDROCHLORIDE 25 mg/5 mL
INACTIVE INGREDIENTS: SUCRALOSE; ANHYDROUS CITRIC ACID; SORBITOL; SODIUM BENZOATE; GLYCERIN; WATER; PROPYLENE GLYCOL; XYLITOL; CARBOXYMETHYLCELLULOSE

Calmco Adult Sleep Aid

Drug Facts

.

Active Ingredient and Purpose

.

Active ingredient (in each 10 mL vial) | Purpose
Diphenhydramine HCl 25 mg............... | Nighttime sleep-aid

Uses

- for the relief of occasional sleeplessness
- reduces time to fall asleep if you have difficulty falling asleep

Warnings

.

Do not use

- with any other product containing diphenhydramine, even one used on skin
- on children under 12 years of age

Ask a doctor before use if you

- have a breathing problem such as emphysema or chronic bronchitis
- glaucoma
- have trouble urinating due to an enlarged prostate gland
- are taking sedatives or tranquilizers

When using this product

avoid consuming alcohol beverages

Stop use and ask a doctor if

- sleeplessness persists continuously for more than 2 weeks.Insomnia may be a symptom of a serious underlying medical illness.

If pregnant or breastfeeding,

ask a healthcare professional before use

KEEP OUT OF REACH OF CHILDREN.

In case of accidental overdose, get medical help or contact a Poison Control Center right away (1-800-222-1222).

Directions

- do not take more than directed
- follow the “Easy to Use” instructions on pouch

Age | Dose
Adults and children 12 years and older | take 2 vials at bedtime, if needed
children under 12 years | do not use

Other information

- each 10 mL vial contains: sodium 4 mg
- store between 68-77°F (20-25°C)
- do not use if pouch has been torn open or vial is punctured or open

Inactive ingredients

Anhydrous citric acid, carboxymethylcellulose, flavors, glycerin, propylene glycol, sodium benzoate, sorbitol solution, sucralose, water, xylitol

Questions or comments?

+1 941-203-4590 (M-F) 9am-5pm EST or visit www.calmco.com

Distributed by: CalmCo LLC, Sarasota, FL 34240

Made in Dominican Republic